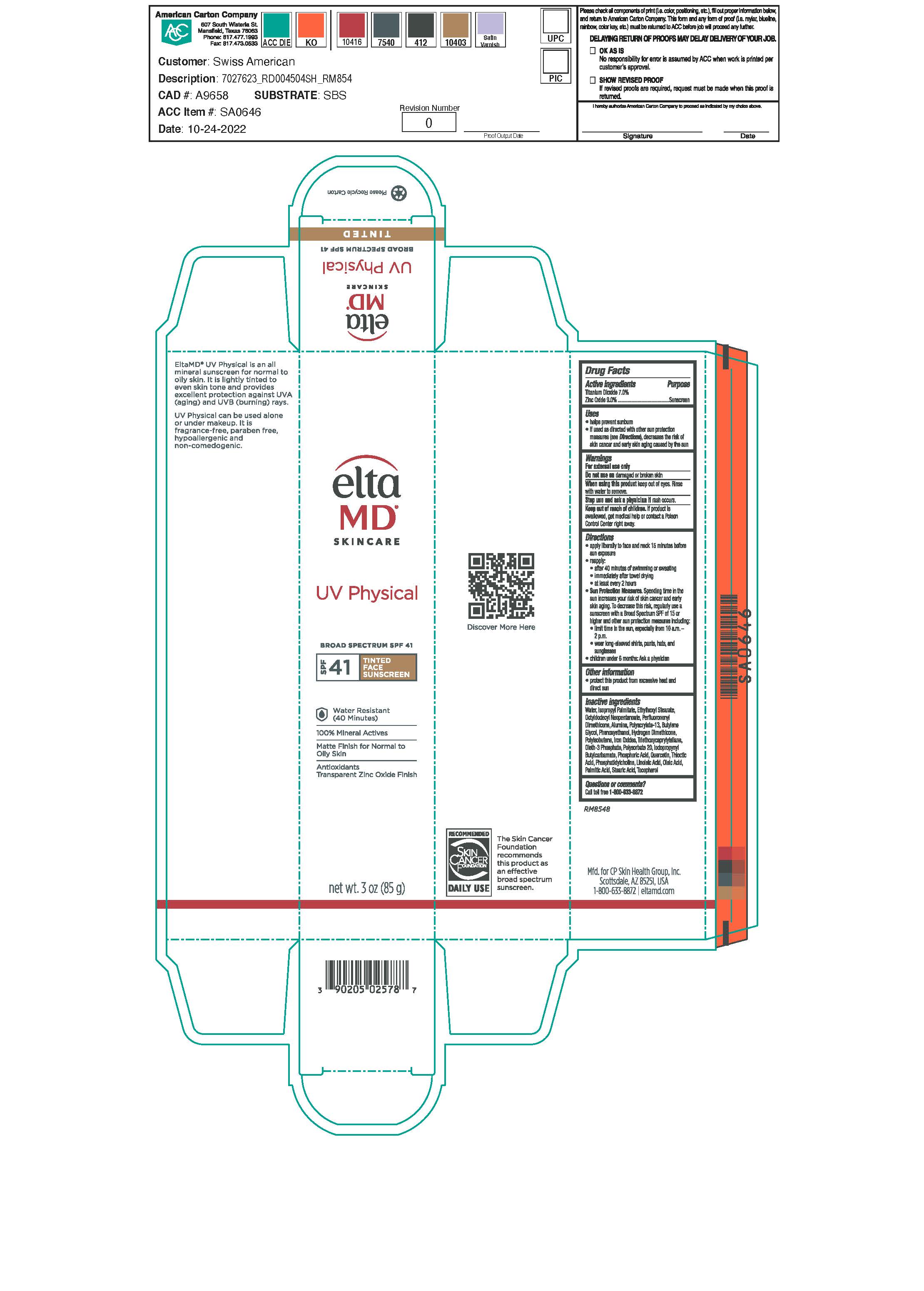 DRUG LABEL: EltaMD UV Physical SPF41
NDC: 72043-2578 | Form: LOTION
Manufacturer: CP Skin Health Group, Inc.
Category: otc | Type: HUMAN OTC DRUG LABEL
Date: 20231109

ACTIVE INGREDIENTS: ZINC OXIDE 90 g/1000 g; TITANIUM DIOXIDE 70 g/1000 g
INACTIVE INGREDIENTS: WATER; SODIUM HYDROXIDE; CITRIC ACID MONOHYDRATE; BUTYLENE GLYCOL; IODOPROPYNYL BUTYLCARBAMATE; PHENOXYETHANOL; ISOPROPYL PALMITATE; OCTYL STEARATE; OCTYLDODECYL NEOPENTANOATE; OLETH-3 PHOSPHATE; TRIETHOXYCAPRYLYLSILANE; ALUMINUM OXIDE; HYDROGEN DIMETHICONE (13 CST); FERRIC OXIDE RED; FERRIC OXIDE YELLOW; FERROSOFERRIC OXIDE; POLYISOBUTYLENE (1000 MW); POLYSORBATE 20; THIOCTIC ACID; LECITHIN, SOYBEAN; QUERCETIN; LINOLEIC ACID

EltaMD UV Physical SPF41

Warnings

For external use only Do not use on damaged or broken skin When using this product keep out of eyes Stop use and ask a physician if rash occurs Keep out of reach of children. If product is swallowed, get medical help or contact a Poison Control Center right away.

Active Ingredients

Zinc Oxide 9.0% Sunscreen
Titanium Dioxide 7.0% Sunscreen

Uses

Helps prevent sunburn if used as directed with other sun protection measures (See Directions), decreases the risk of skin cancer and early skin aging caused by the sun.

Uses

Helps prevent sunburn if used as directed with other sun protection measures (See Directions), decreases the risk of skin cancer and early skin aging caused by the sun.

Directions

apply liberally 15 minutes before sun exposure reapply: after 40 minutes of swimming or sweating immediately after towel drying at lest every 2 hours Sun Protection Measures: Spending time in the sun increases your risk of skin cancer and early skin aging. To decrease this risk, regularly use a sunscreen with a broad-spectrum SPF of 15 or higher and other sun protection measures including: limit time int he sun, especially from 10 a.m. - 2 p.m. wear long-sleeve shirts, pants, hats and sunglasses children under 6 months: Ask a physician

Inactive Ingredients

Alumina, Butylene Glycol, Citric Acid, Iodopropynyl Butylcarbamate, Iron Oxide, Isopropyl Palmitate, Lecithin, Linoleic Acid, Hydrogen Dimethicone, Octyl Stearate, Octyldodecyl Neopentanoate, Oleth-3 Phosphate, Perfluorononyl Dimethicone, Phenoxyethanol, Polyacrylate 13, Polyisobutene, Polysorbate 20, Purified Water, Quercitin, Sodium Hydroxide, Thioctic Acid, Triethoxycaprylylsilane

KEEP OUT OF REACH OF CHILDREN